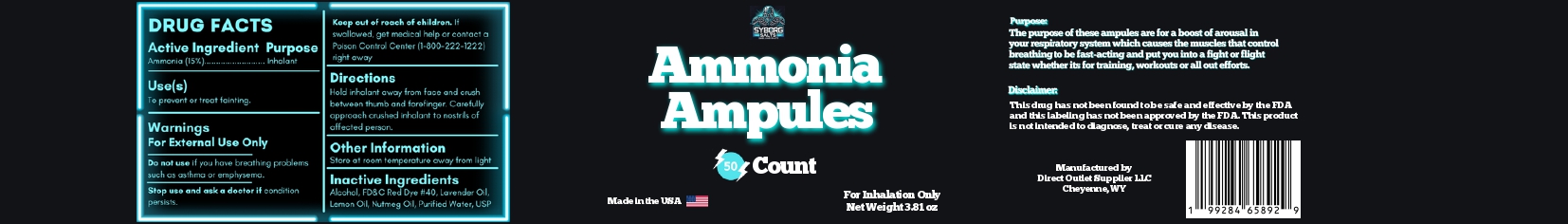 DRUG LABEL: ammonia inhalants
NDC: 85813-003 | Form: INHALANT
Manufacturer: Direct Outlet Supplier LLC
Category: otc | Type: HUMAN OTC DRUG LABEL
Date: 20251127

ACTIVE INGREDIENTS: AMMONIA 15 g/100 mL
INACTIVE INGREDIENTS: ALCOHOL; FD&C RED NO. 4; LAVENDER OIL; LEMON OIL; NUTMEG OIL; WATER

Amonia Ampules

Active Ingredient

Ammonia (15%)

Purpose

Inhalant

Uses

To prevent or treat fainting.

Warnings

For external use only.

Do not use if you have breathing problems such as asthma or emphysema.

Stop use and ask a doctor if condition persists.

Keep out of reach of children. If swallowed get medical help or contact a Poison Control Center (1-800-222-1222) right away.

Directions

Hold inhalant away from face and crush between thumb and forefinger. Carefully approach crushed inhalant to nostrils of affected person.

Other Information

Store at room temperature away from light.

Inactive Ingredients

Alcohol, FD&C Red Dye # 40, Lavender Oil, Lemon Oil, Nutmeg Oil, Purified Water USP.